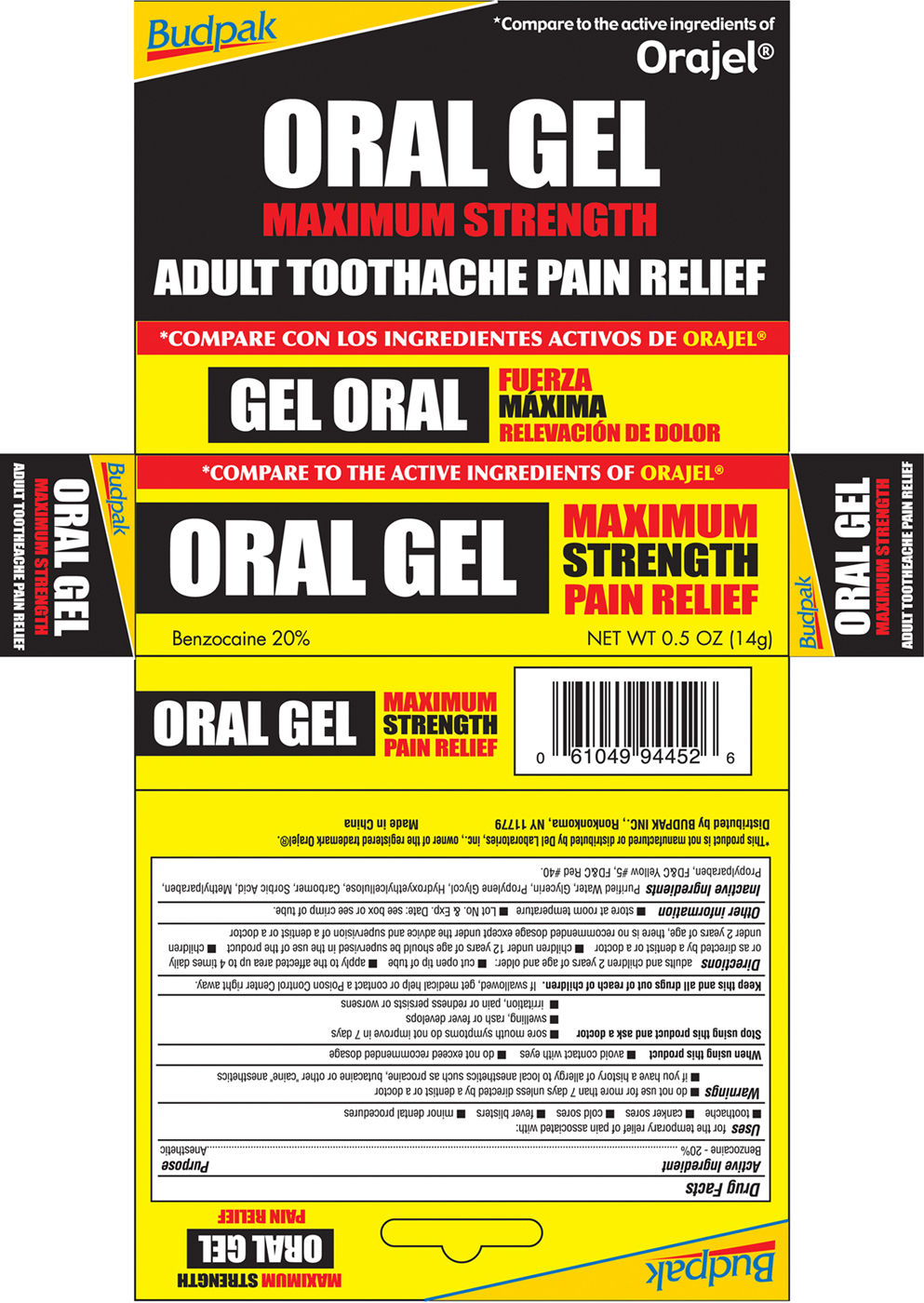 DRUG LABEL: Oral Gel
NDC: 27293-012 | Form: GEL
Manufacturer: Budpak Inc.
Category: otc | Type: HUMAN OTC DRUG LABEL
Date: 20100116

ACTIVE INGREDIENTS: BENZOCAINE 20 g/100 g
INACTIVE INGREDIENTS: WATER; GLYCERIN; PROPYLENE GLYCOL; SORBIC ACID; METHYLPARABEN; PROPYLPARABEN; FD&C YELLOW NO. 5; FD&C RED NO. 40

Drug Facts

Active Ingredient
Benzocaine 20%

Purpose
Anesthetic

INDICATIONS AND USAGE

Uses for the temporary relief of pain associated with:

- toothache
- canker sores
- cold sores
- fever blisters
- minor dental procedures

Warnings

- do not use for more than 7 days unless directed by a dentist or a doctor
- if you have a history of allergy to local anesthetics such as procaine, butacaine or other "caine" anesthetics

When using this product

- avoid contact with the eyes
- do not exceed recommended dosage

Stop using and ask a doctor

- sore mouth symptoms do not improve in 7 days
- swelling, rash or fever develops
- irritation, pain or redness persists or worsens

KEEP OUT OF REACH OF CHILDREN

Keep this and all drugs out of reach of children. If swallowed, get medical help or contact a Poison Control Center right away

DOSAGE AND ADMINISTRATION

Directions adults and children 2 years of age and older:

- cut open tip of tube
- apply to the affected area up to 4 times daily or as directed by a dentist or doctor
- children under 12 years of age should be supervised in the use of the product
- children under 2 years of age, there is no recommended dosage except under the advice and supervision of a dentist or a doctor

Other information

- store at room temperature
- Lot No. and Exp. Date: see box or see crimp of tube

INACTIVE INGREDIENT

Inactive Ingredients Purified water, Glycerin, Propylene Glycol, Hydroxyethylcellulose, Carbomer, Sorbic Acid, Methylparaben, Propylparaben, FDC Yellow 5, FDC Red 40

Package Label